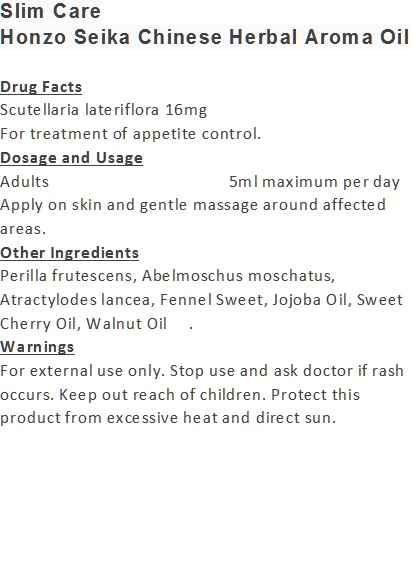 DRUG LABEL: Slim Care
NDC: 71263-9904 | Form: OIL
Manufacturer: NIC CO., LTD.
Category: otc | Type: HUMAN OTC DRUG LABEL
Date: 20170101

ACTIVE INGREDIENTS: SCUTELLARIA LATERIFLORA 18 mg/100 mL
INACTIVE INGREDIENTS: ABELMOSCHUS MOSCHATUS SEED; SWEET CHERRY SEED OIL; WALNUT OIL; JOJOBA OIL; FENNEL OIL; ATRACTYLODES LANCEA ROOT OIL; PERILLA FRUTESCENS LEAF OIL

Drug Facts

Scutellaria lateriflora 16mg

Use

For treatment of appetite control.

Dosage Suggestion

Adults 5ml maximum per day

INACTIVE INGREDIENT

Other Ingredients

Perilla frutescens, Abelmoschus moschatus, Atractylodes lancea, Fennel Sweet, Jojoba Oil, Sweet Cherry Oil, Walnut Oil.

Directions

Apply on skin and gentle massage around affected area.

Warnings

For external use only. Stop use and ask doctor if rash occurs. Keep out reach of children.

Other Information

Protect this product from excessive heat

and direct sun.

Warnings

For external use only. Stop use and ask doctor if rash occurs. Keep out reach of children.